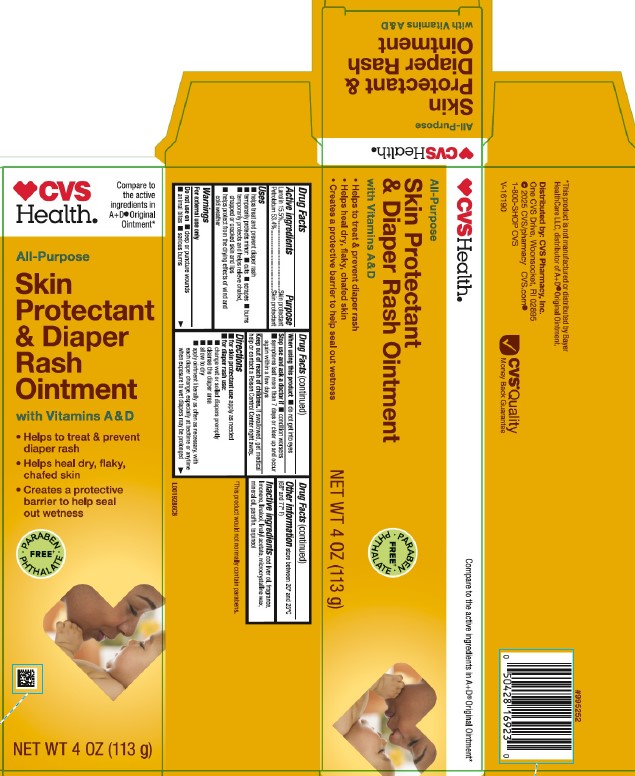 DRUG LABEL: Lanolin, Petrolatum
NDC: 69842-488 | Form: OINTMENT
Manufacturer: CVS Pharmacy, Inc.
Category: otc | Type: HUMAN OTC DRUG LABEL
Date: 20260202

ACTIVE INGREDIENTS: LANOLIN 155 mg/1 g; PETROLATUM 534 mg/1 g
INACTIVE INGREDIENTS: COD LIVER OIL; LIMONENE, (+)-; LINALOOL, (+/-)-; LINALYL ACETATE; MICROCRYSTALLINE WAX; MINERAL OIL; PARAFFIN; TERPINEOL

CVS 013.001/013AC
Vitamin A&D Ointment

Active ingredients

Lanolin 15.5%

Petrolatum 53.4%

Purpose

Skin protectant

Uses

- helps treat and prevent diaper rash
- temporarily protects minor: - cuts - scrapes - burns
- temporarily protects and helps relieve chafed, chapped or cracked skin and lips
- helps protect from the drying effects of wind and cold weather

Warnings

For external use only

Do not use on

- deep or puncture wounds
- animal bites
- serious burns

When using this product

- do not get into eyes

Stop use and ask a doctor if

- condition worsens
- symptoms last more than 7 days or clear up and occur again within a few days

Keep out of reach of children.

If swallowed, get medical help or contact a Poison Control Center right away.

Directions

- for skin protectant use: apply as needed
- for diaper rash use:
- change wet or soiled diapers promptly
- cleanse the diaper area
- allow to dry
- apply ointment liberally as often as necessary, with each diaper change, especially at bedtime or anytime when exposure to wet diapers may be prolonged

other information

store between 20º and 25ºC (68º and 77º F)

Inactive ingredients

cod liver oil, fragrance, limonene, linalool, linalyl acetate, microcrystalline wax, mineral oil, paraffin, terpineol

ADVERSE REACTION

†This product would not normally contain parabens.

*This product is not manufactured or distributed by Bayer HealthCare LLC, distributor of A+DOriginal Ointment.

Distributed by: CVS Pharmacy, Inc.

One CVS Drive, Woonsocket, RI 02895

©2025 CVS/pharmacy CVS.com

1-800-SHOP CVS

V-16190

CVS Quality Money Back Guarantee

principal display panel

CVS Health®

Compare to the active ingredients in A + D®Original Ointment*

All-Purpose

Skin Protectant & Diaper Rash Ointment

with Vitamins A & D

- Helps to treat & prevent diaper rash
- Helps heal dry, flaky, chafed skin
- Creates a protective barrier to help seal out wetness

PARABEN-PHTHALATE FREE†

NET WT 4 OZ (113 g)